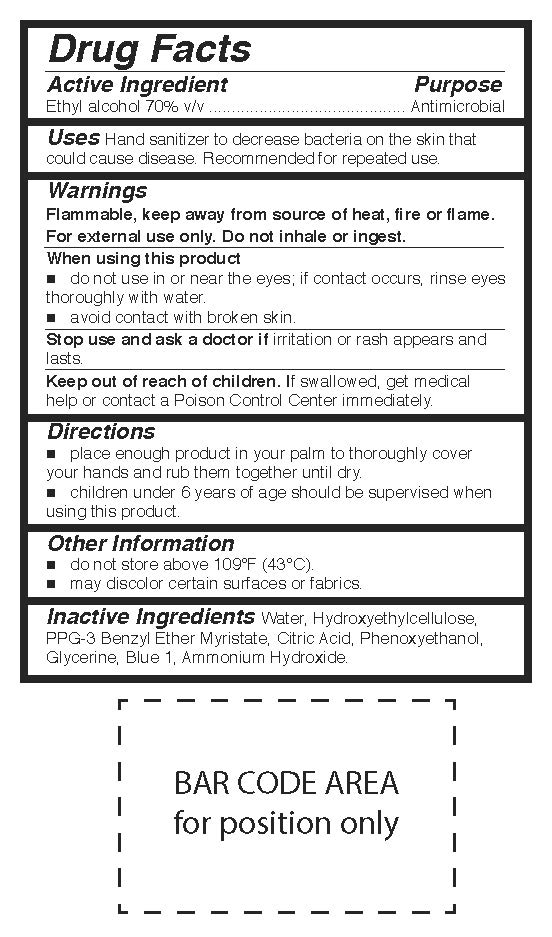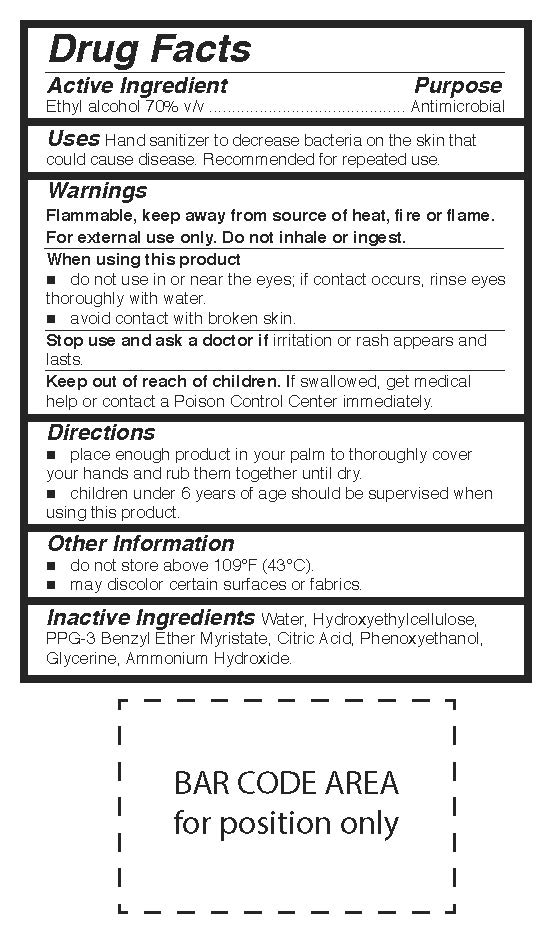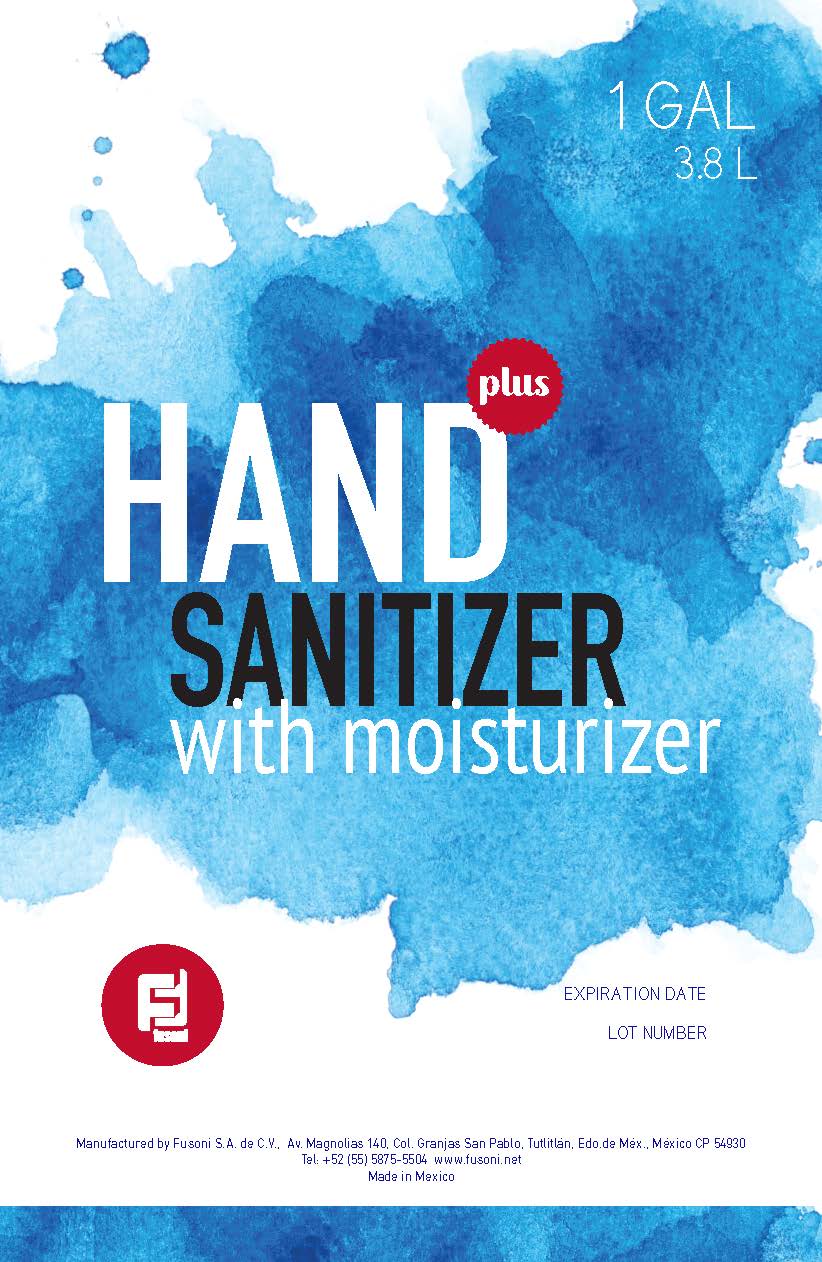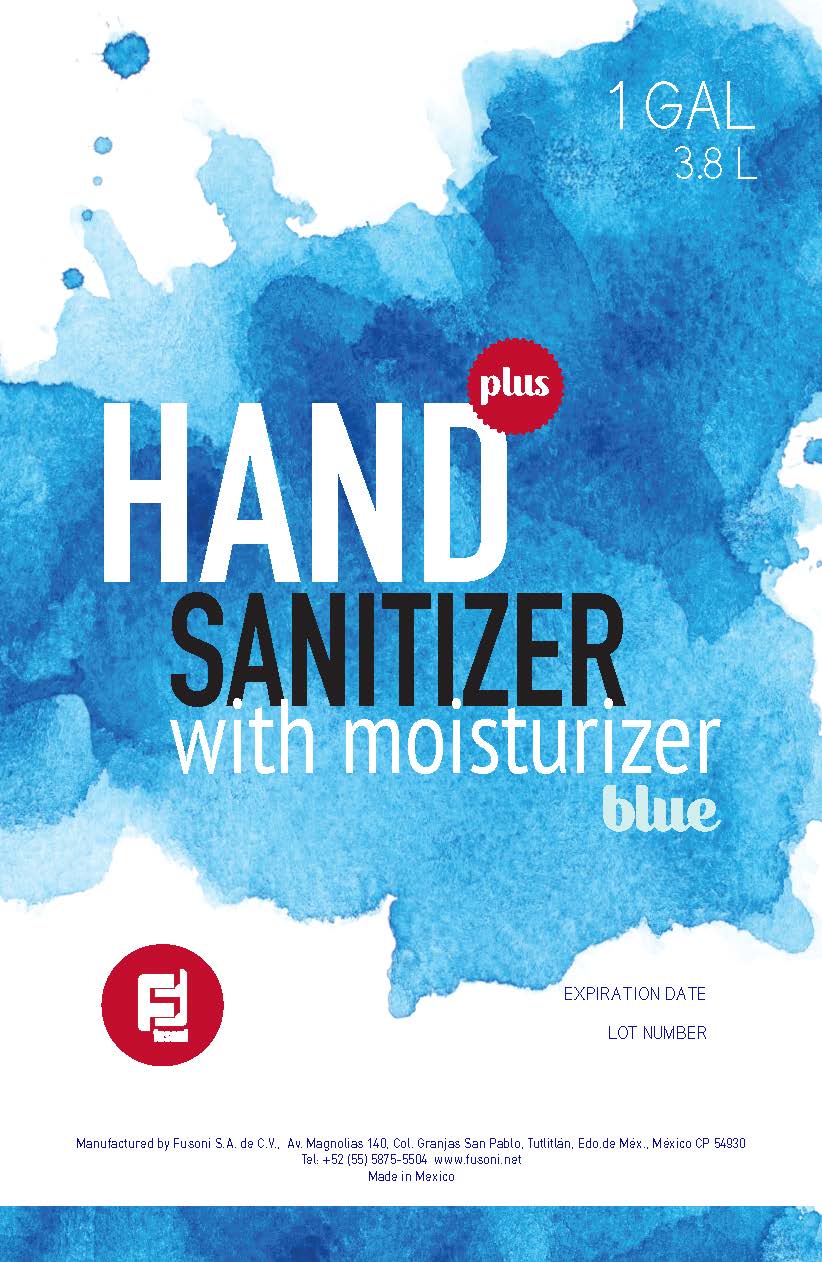 DRUG LABEL: Fusoni Hand Sanitizer with Moisturizer Plus Blue
NDC: 79380-012 | Form: GEL
Manufacturer: Fusoni S.A. de C.V.
Category: otc | Type: HUMAN OTC DRUG LABEL
Date: 20200707

ACTIVE INGREDIENTS: ALCOHOL 0.7 L/1 L
INACTIVE INGREDIENTS: FD&C BLUE NO. 1; HYDROXYETHYL CELLULOSE (4000 MPA.S AT 1%); PPG-3 BENZYL ETHER MYRISTATE; ANHYDROUS CITRIC ACID; WATER; GLYCERIN; PHENOXYETHANOL; AMMONIA

Hand Sanitizer Plus products listing

Active Ingredient

Ethyl alcohol 70% v/v

Purpose

Antimicrobial

Uses

Hand sanitizer to decrease bacteria on the skin that could cause disease. Recommended for repeated use.

Warnings

Flammable, keep away from source of heat, fire or flame.
For external use only. Do not inhale or ingest.

When using this product

do not use in or near the eyes; if contact occurs, rinse eyes
thoroughly with water.

avoid contact with broken skin.

Stop use and ask a doctor if irritation or rash appears and lasts.

Keep out of reach of children

If swallowed, get medical help or contact a Poison Control Center immediately.

Directions

place enough product in your palm to thoroughly cover your hands and rub them together until dry.
children under 6 years of age should be supervised when using this product.

Other information

do not store above 109°F (43°C).
may discolor certain surfaces or fabrics.

Inactive ingredients

Product 011 "DRUG FACTS Fusoni Hand Sanitizer Plus.jpg":

Water, Hydroxyethylcellulose, PPG-3 Benzyl Ether Myristate, Citric Acid, Phenoxyethanol, Glycerine, Ammonium Hydroxide.

Product 012 "DRUG FACTS Fusoni Hand Sanitizer Plus Blue.jpg":

Water, Hydroxyethylcellulose, PPG-3 Benzyl Ether Myristate, Citric Acid, Phenoxyethanol, Glycerine, Blue 1, Ammonium Hydroxide.

PACKAGE LABEL

3.8 L NDC: 79380-011-12

PACKAGE LABEL

3.8 L NDC: 79380-012-12